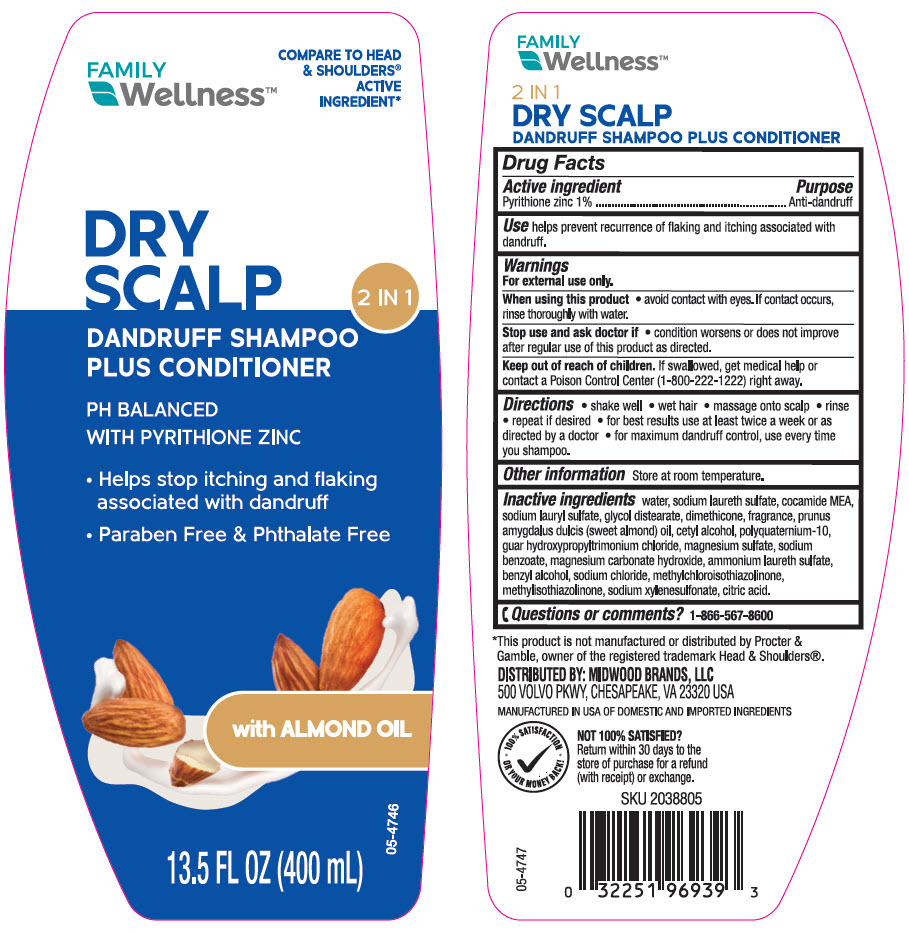 DRUG LABEL: FAMILY WELLNESS DRY SCALP 2 IN 1 DANDRUFF PLUS CONDITIONER
NDC: 55319-691 | Form: SHAMPOO
Manufacturer: FAMILY DOLLAR SERVICES INC
Category: otc | Type: HUMAN OTC DRUG LABEL
Date: 20251120

ACTIVE INGREDIENTS: Pyrithione Zinc 10 mg/1 mL
INACTIVE INGREDIENTS: Water; SODIUM LAURETH-3 SULFATE; COCO MONOETHANOLAMIDE; Sodium Lauryl Sulfate; Glycol Distearate; Dimethicone; ALMOND OIL; Cetyl Alcohol; POLYQUATERNIUM-10 (30000 MPA.S AT 2%); GUAR HYDROXYPROPYLTRIMONIUM CHLORIDE; MAGNESIUM SULFATE, UNSPECIFIED FORM; Sodium Benzoate; Magnesium Carbonate Hydroxide; AMMONIUM LAURETH-5 SULFATE; Benzyl Alcohol; Sodium Chloride; Methylchloroisothiazolinone; Methylisothiazolinone; Sodium Xylenesulfonate; CITRIC ACID MONOHYDRATE

FAMILY WELLNESS™ DRY SCALP 2 IN 1 DANDRUFF SHAMPOO PLUS CONDITIONER
Anti-Dandruff

Drug Facts

Active ingredient

Pyrithione zinc 1 %

Purpose

Anti-dandruff

Use

helps prevent recurrence of flaking and itching associated with dandruff.

Warnings

For external use only.

When using this product avoid contact with the eyes. If contact occurs, rinse eyes thoroughly with water.

Stop use and ask a doctor if condition worsens or does not improve after regular use of this product as directed.

Keep out of reach of children. If swallowed, get medical help or contact a Poison Control Center (1-800-222-1222) right away.

Directions

- shake well
- wet hair
- massage onto scalp
- rinse
- repeat if desired
- for best results use at least twice a week or as directed by a doctor
- for maximum dandruff control, use every time you shampoo.

Other information

store at room temperature

Inactive ingredients

water, sodium laureth sulfate, cocamide MEA, sodium lauryl sulfate, glycol distearate, dimethicone, fragrance, prunus amygdalus dulcis (sweet almond) oil, cetyl alcohol, polyquaternium-10, guar hydroxypropyltrimonium chloride, magnesium sulfate, sodium benzoate, magnesium carbonate hydroxide, ammonium laureth sulfate, benzyl alcohol, sodium chloride, methylchloroisothiazolinone, methylisothiazolinone, sodium xylenesulfonate, citric acid.

Questions or comments?

1-866-567-8600

DISTRIBUTED BY: MIDWOOD BRANDS, LLC
500 VOLVO PKWY, CHESAPEAKE, VA 23320 USA

PRINCIPAL DISPLAY PANEL - 400 mL Bottle Label

FAMILY
Wellness™

COMPARE TO HEAD
& SHOULDERS®
ACTIVE
INGREDIENT*

DRY
SCALP
2 IN 1
DANDRUFF SHAMPOO
PLUS CONDITIONER

PH BALANCED
WITH PYRITHIONE ZINC

- Helps stop itching and flaking
  associated with dandruff
- Paraben Free & Phthalate Free

with ALMOND OIL

13.5 FL OZ (400 mL)

05-4746

Family Wellness Dry Scalp